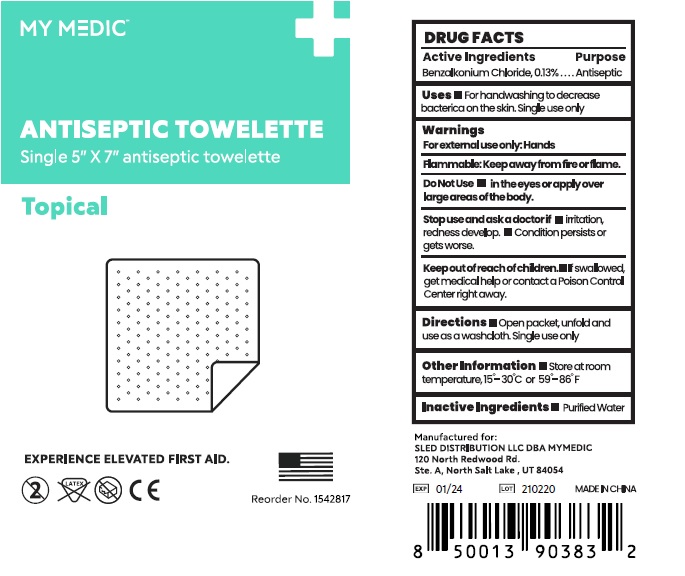 DRUG LABEL: Antiseptic Towelette
NDC: 81417-010 | Form: CLOTH
Manufacturer: Sled Distribution, LLC
Category: otc | Type: HUMAN OTC DRUG LABEL
Date: 20221102

ACTIVE INGREDIENTS: BENZALKONIUM CHLORIDE 0.13 g/100 mL
INACTIVE INGREDIENTS: WATER

MY MEDIC
ANTISEPTIC TOWELETTE

Active Ingredient

BENZALKONIUM CHLORIDE 0.13%

Purpose

Antiseptic

USE

- For handwashing to decrease bacterica on the skin. Signle use only.

Warning

- Flammable, keep away from fire or flame.
- For external use only.

Do not use

- in the eyes or apply over large areas of the body.
- Stop use and ask a doctor,
- Irritaion , redness develop.
- Condition persists or gets worse.

Other Information：

- Store at room temperature, 15-30 ℃ or 59-86℉.

KEEP OUT OF REACH OF CHILDREN

●If swallowed, get medical help or contact a Poison Contrl Center right away.

Directions

- Open packet, unfold and use as a washcloth. Single use only.

Inactive ingredients

Purified Water